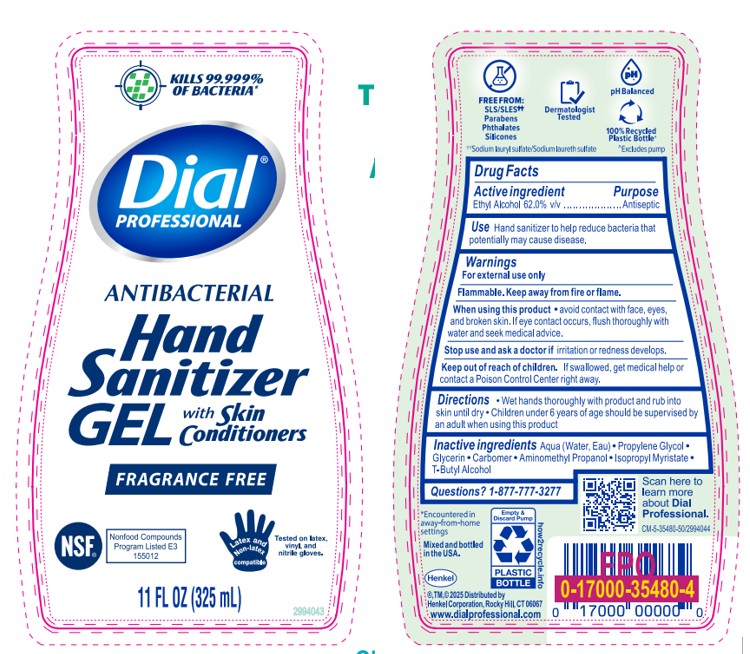 DRUG LABEL: Dial Professional Gel Sanitizer
NDC: 54340-136 | Form: GEL
Manufacturer: Henkel Corporation
Category: otc | Type: HUMAN OTC DRUG LABEL
Date: 20251211

ACTIVE INGREDIENTS: ALCOHOL 60.14 mL/100 mL
INACTIVE INGREDIENTS: WATER 38.19 mL/100 mL

Dial Professional Gel Hand Sanitizer
Dial Professional Hand Sanitizer Gel 11 Fl Oz (12)
Dial Professional Antibacterial Hand Sanitizer Gel

Dial Hand Sanitzer (Gel/Foaming)

Dial Professional Gel Hand Sanitizer

Active Ingredient: Ethyl Alcohol 62.0% v/v Purpose: Antiseptic

Warnings

Warnings For external use only
Flammable. Keep away from fire or flame.

When using this product•Avoid contact with face, eyes, and broken skin. •If eye contact occurs, flush thoroughly with water and seek medical advice.ORWhen using this productavoid contact with face, eyes, and broken skin.If eye contact occurs, flush thoroughly with water and seek medical advice.
Stop use and ask a doctor if•Irritation or redness developsORStop use and ask a doctor ifirritation or redness develops
Keep out of reach of children. •If swallowed, get medical help or contact a Poison Control Center right away

DOSAGE AND ADMINISTRATION

Use(s)Hand sanitizer to help reduce bacteria thatpotentially may cause disease

INDICATIONS AND USAGE

Use(s)Hand sanitizer to help reduce bacteria that potentially may cause disease

Inactive ingredients Aqua (Water, Eau) · Propylene Glycol ·

Glycerin . Carbomer . Aminomethyl Propanol . Isopropyl Myristate .
T-Butyl Alcohol